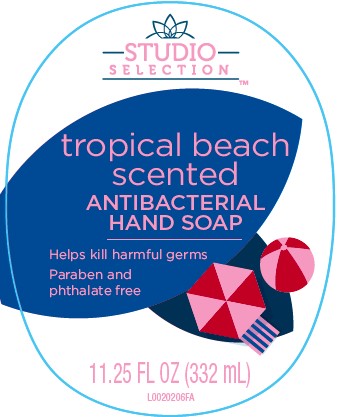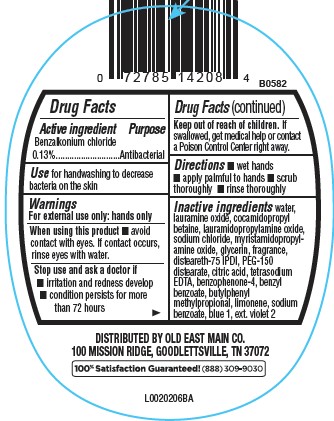 DRUG LABEL: Moisturizing Antibacterial
NDC: 55910-969 | Form: SOAP
Manufacturer: Old East Main Co.
Category: otc | Type: HUMAN OTC DRUG LABEL
Date: 20250815

ACTIVE INGREDIENTS: BENZALKONIUM CHLORIDE 1.3 g/1 mL
INACTIVE INGREDIENTS: BUTYLPHENYL METHYLPROPIONAL; LIMONENE, (+)-; DOCUSATE SODIUM/SODIUM BENZOATE; FD&C BLUE NO. 1; EXT. D&C VIOLET NO. 2; WATER; LAURAMINE OXIDE; COCAMIDOPROPYL BETAINE; LAURAMIDOPROPYLAMINE OXIDE; SODIUM CHLORIDE; MYRISTAMIDOPROPYLAMINE OXIDE; GLYCERIN; DISTEARETH-75 ISOPHORONE DIISOCYANATE; PEG-150 DISTEARATE; CITRIC ACID MONOHYDRATE; EDETATE SODIUM; SULISOBENZONE; SODIUM BENZOATE; BENZYL BENZOATE

Studio Selection D03.000/D03AA
Tropical Scented Antibacterial Hand Soap

Active ingredient

Benzalkonium chloride 0.13%

Purpose

Antibacterial

Use

for handwashing to decrease bacteria on the skin

Warnings

For external use only: hands only

When using this product

- avoid contact with eyes. If contact occurs, rinse eyes thoroughly with water.

Stop use and ask a doctor if

- irritation and redness develop
- condition persists for more than 72 hours

Keep out of reach of children.

If swallowed, get medical help or contact a Poison Control Center right away.

Directions

- wet hands
- apply palmful to hands
- scrub thoroughly
- rinse thoroughly

Inactive ingredients

water, lauramine oxide, cocamidopropyl betaine, lauramidopropylamine oxide, sodium chloride, myristamidopropylamine oxide, glycerin, fragrance, disteareth-75 IPDI, PEG-150 distearate, citric acid, tetrasodium EDTA, benzophenone-4, benzyl benzoate, butylphenyl methylpropional, limonene, sodium benzoate, blue 1, ext. violet 2

Adverse reactions

DISTRIBUTED BY OLD EAST MAIN CO.

100 MISSION RIDGE, GOODLETTSVILLE, TN 37072

100% Satisfaction Guaranteed! (888)309-9030

principal display panel

STUDIO SELECTION™

tropical beach

scented

ANTIBACTERIAL HAND SOAP

Helps kill harmful germs

Paraben and phthalate free

11.25 FL OZ (332 mL)